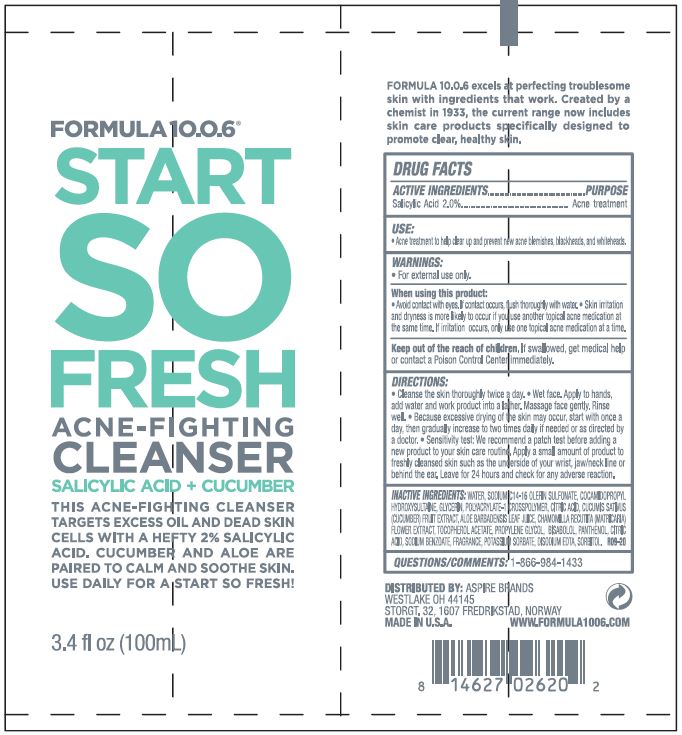 DRUG LABEL: START SO FRESH
NDC: 70626-105 | Form: GEL
Manufacturer: ASPIRE BRANDS INC
Category: otc | Type: HUMAN OTC DRUG LABEL
Date: 20241206

ACTIVE INGREDIENTS: SALICYLIC ACID 2 g/100 mL
INACTIVE INGREDIENTS: WATER; SODIUM C14-16 OLEFIN SULFONATE; COCAMIDOPROPYL HYDROXYSULTAINE; GLYCERIN; AMMONIUM ACRYLOYL DIMETHYLTAURATE/METHACRYLATE, DIMETHYLACRYLAMIDE AND METHACRYLIC ACID COPOLYMER, PPG-3 GLYCERYL TRIACRYLATE CROSSLINKED (100000 MW); ANHYDROUS CITRIC ACID; CUCUMBER; ALOE VERA LEAF; CHAMOMILE; .ALPHA.-TOCOPHEROL ACETATE; PROPYLENE GLYCOL; .ALPHA.-BISABOLOL, (+)-; PANTHENOL; SODIUM BENZOATE; POTASSIUM SORBATE; EDETATE DISODIUM; SORBITOL

ASPIRE BRANDS - FORMULA 10.0.6 START SO FRESH ACNE-FIGHTING CLEANSER (70626-105)

ACTIVE INGREDIENT

SALICYLIC ACID 2%

PURPOSE

ACNE TREATMENT

USE

ACNE TREATMENT TO HELP CLEAR UP AND PREVENT NEW ACNE BLEMISHES, BLACKHEADS, AND WHITEHEADS.

WARNINGS

- FOR EXTERNAL USE ONLY

WHEN USING THIS PRODUCT:

- AVOID CONTACT WITH EYES. IF CONTACT OCCURS, FLUSH THOROUGHLY WITH WATER.
- SKIN IRRITATION AND DRYNESS IS MORE LIKELY TO OCCUR IF YOU USE ANOTHER TOPICAL ACNE MEDICATION AT THE SAME TIME. IF IRRITATION OCCURS, ONLY USE ONE TOPICAL ACNE MEDICATION AT A TIME.

KEEP OUT OF REACH OF CHILDREN. IF SWALLOWED, GET MEDICAL HELP OR CONTACT A POISON CONTROL CENTER RIGHT AWAY.

DIRECTIONS

- CLEAN THE SKIN THOROUGHLY TWICE A DAY.
- WET FACE. APPLY TO HANDS, ADD WATER AND WORK PRODUCT INTO A LATHER. MASSAGE FACE GENTLY. RINSE WELL.
- BECAUSE EXCESSIVE DRYING OF THE SKIN MAY OCCUR, START WITH ONCE A DAY, THEN GRADUALLY INCREASE TO TWO TIMES DAILYIF NEEDED OR AS DIRECTED BY A DOCTOR.
- SENSITIVITY TEST: WE RECOMMEND A PATCH TEST BEFORE ADDING A NEW PRODUCT TO YOUR SKIN CARE ROUTINE. APPLY A SMALL AMOUNT OF PRODUCT TO FRESHLY CLEANSED SKIN SUCH AS THE UNDERSIDE OF YOUR WRIST, JAW/NECK LINE OR BEHIND THE EAR. LEAVE FOR 24 HOURS AND CHECK FOR ANY ADVERSE REACTION.

INACTIVE INGREDIENTS

WATER, SODIUM C14-16 OLEFIN SULFONATE, COCAMIDOPROPYL HYDROXYSULTANE, GLYCERIN, POLYACRYLATE-1 CROSSPOLYMER, CITRIC ACID, CUCUMIS SATIVUS (CUCUMBER) FRUIT EXTRACT, ALOE BARBADENSIS LEAF JUICE, CHAMOMILLA RECUTITA (MATRICARIA) FLOWER EXTRACT, TOCPHEROL ACETATE, PROPYLENE GLYCOL, BISABOLOL, PANTHENOL, CITRIC ACID, SODIUM BENZOATE, FRAGRANCE, POTASSIUM SORBATE, DISODIUM EDTA, SORBITOL

QUESTIONS/COMMENTS:

1-866-984-1433